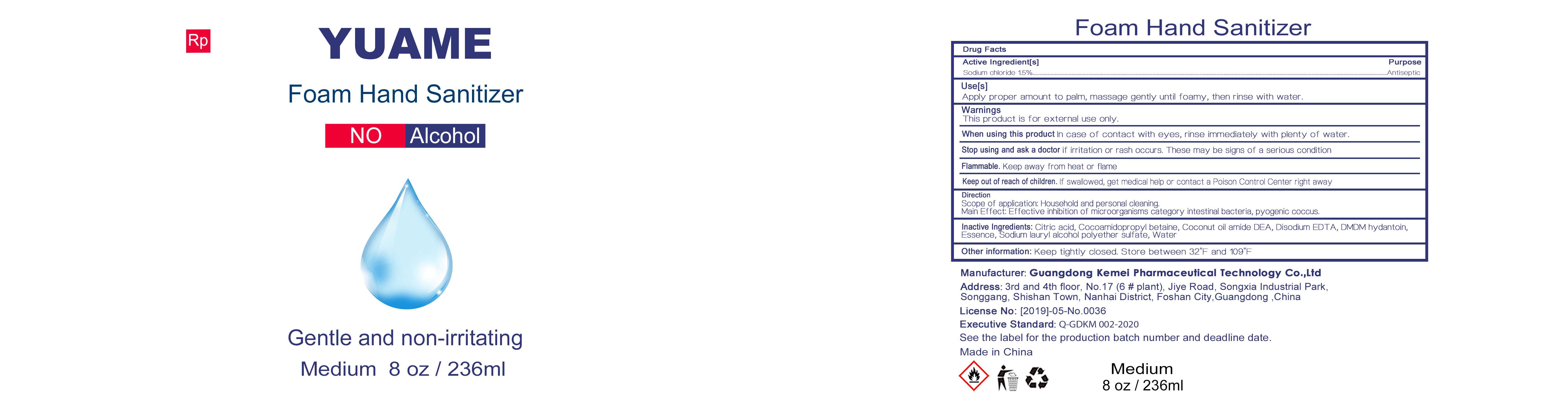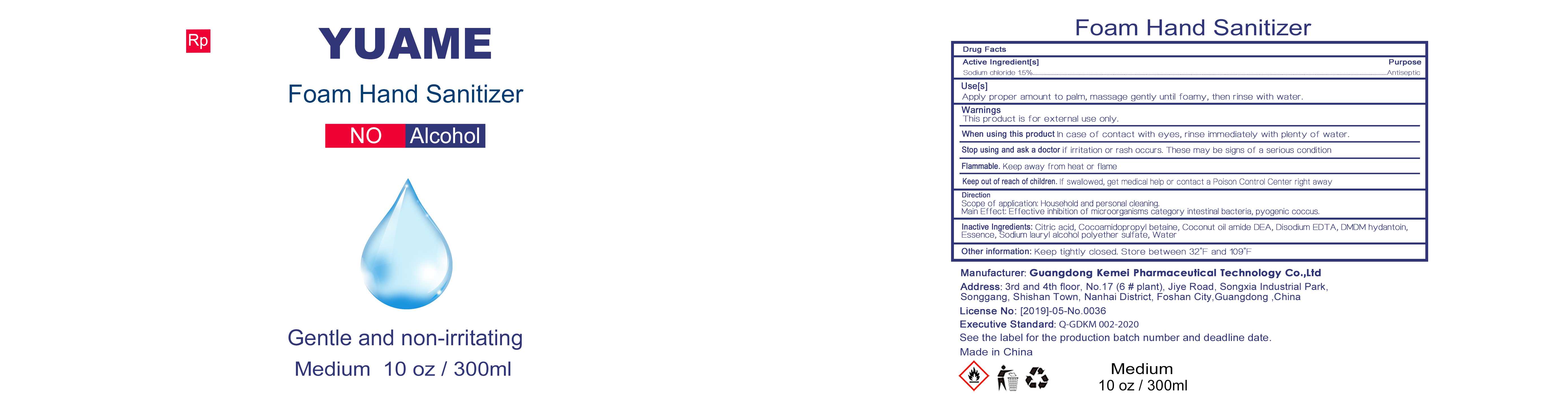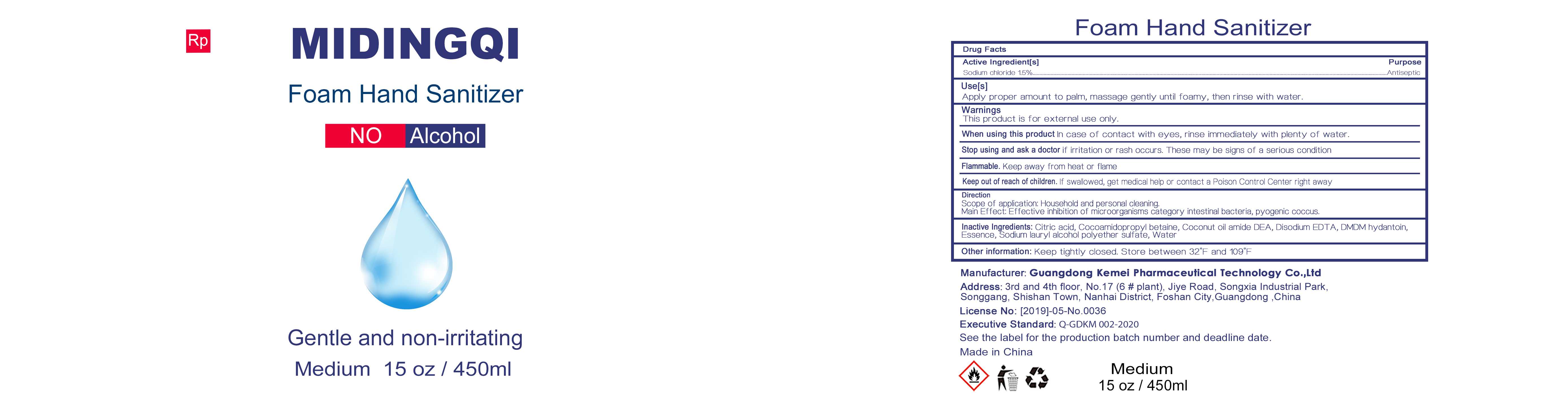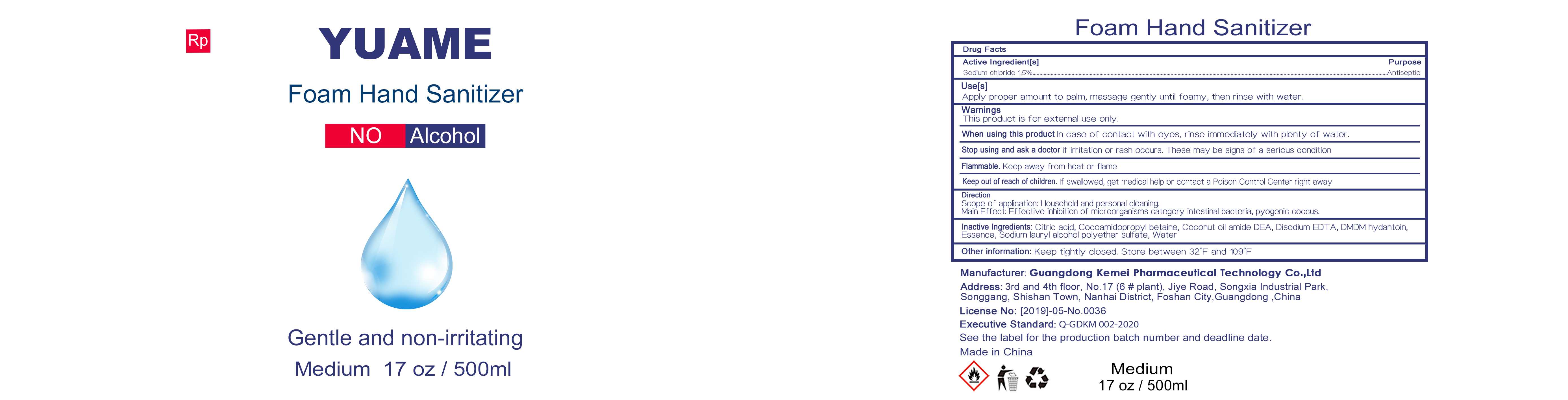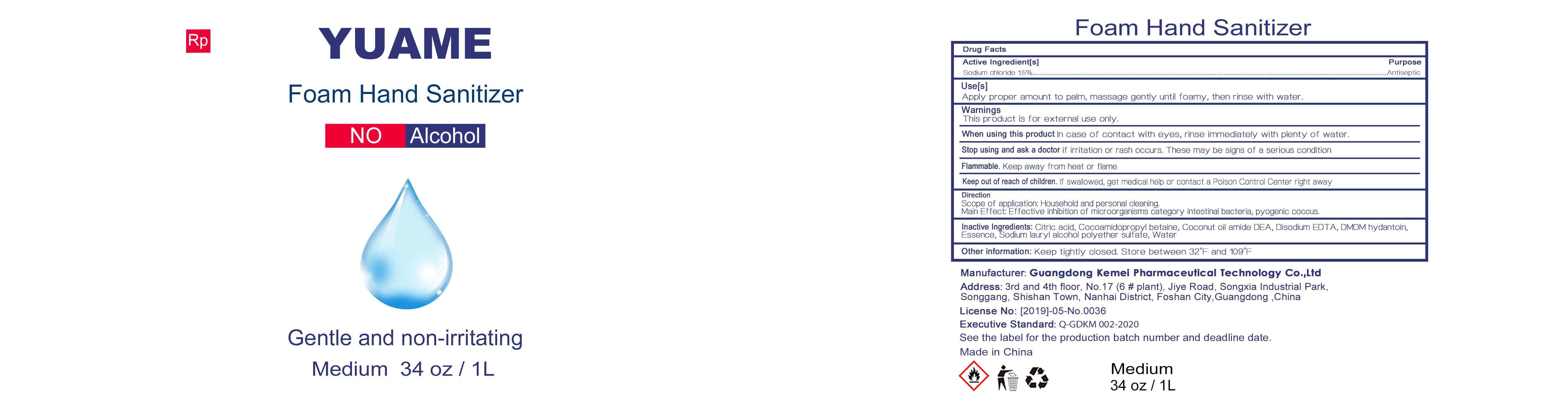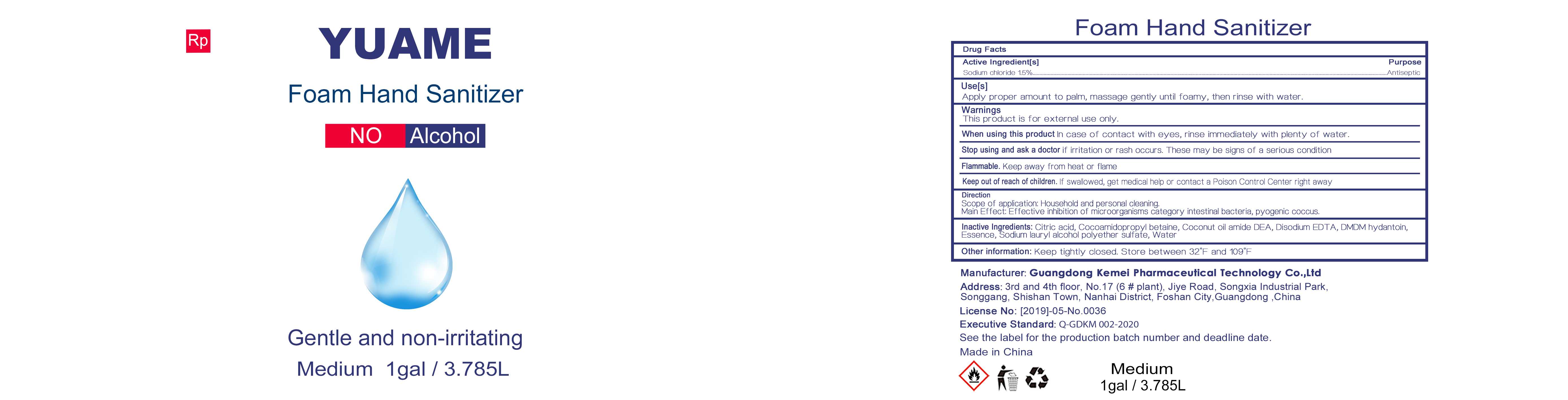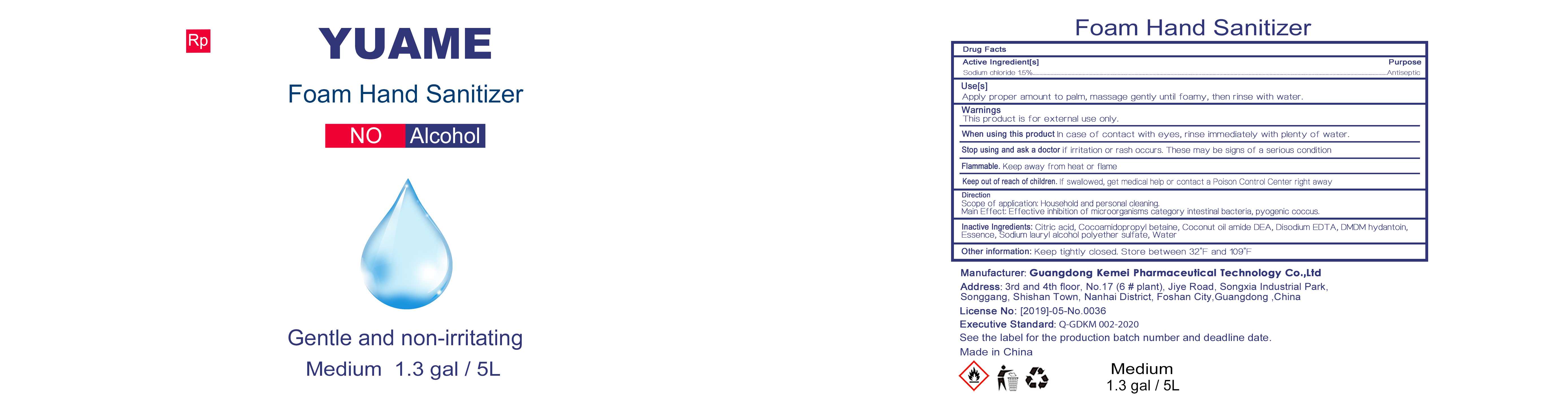 DRUG LABEL: Foam Hand Sanitizer
NDC: 75132-013 | Form: LIQUID
Manufacturer: Guangdong Kemei Pharmaceutical Technology Co., Ltd.
Category: otc | Type: HUMAN OTC DRUG LABEL
Date: 20200919

ACTIVE INGREDIENTS: SODIUM CHLORIDE 1.5 g/100 mL
INACTIVE INGREDIENTS: WATER; COCO DIETHANOLAMIDE; COCAMIDOPROPYL BETAINE; SODIUM LAURETH SULFATE; DMDM HYDANTOIN; CITRIC ACID MONOHYDRATE; EDETATE DISODIUM ANHYDROUS; METHYL BENZOATE

75132-013
Foam Hand Sanitizer

ACTIVE INGREDIENTS

Sodium chloride 1.5%

Purpose

Antiseptic

Uses

Apply proper amount to palm, massage gently until foamy, then rinse with water.

Warnings

This product is for external use only.

When using this product In case of contact with eyes, rinse immediately with plenty of water.

Stop using and ask a doctor if irritation or rash occurs. These may be signs of a serious condition
Flammable. Keep away from heat or flame

Keep out of reach of children. If swallowed, get medical help or contact a Poison Control Center right away

DO NOT USE

/

When using this product In case of contact with eyes, rinse immediately with plenty of water.

Stop using and ask a doctor if irritation or rash occurs. These may be signs of a serious condition
Flammable. Keep away from heat or flame

Keep out of reach of children. If swallowed, get medical help or contact a Poison Control Center right away

STOP USE

Stop using and ask a doctor if irritation or rash occurs. These may be signs of a serious condition
Flammable. Keep away from heat or flame

Keep out of reach of children. If swallowed, get medical help or contact a Poison Control Center right away

Directions

Scope of application: Household and personal cleaning.
Main Effect Effective inhibition of microorganisms category intestinal bacteria, pyogenic coccus.

Other information

Keep tightly closed. Store between 32°F and 109°F

Inactive ingredients

Citric acid, Cocoamidopropyl betaine, Coconut oil amide DEA, Disodium EDTA, DMDM hydantoin, Essence, Sodium lauryl alcohol polyether sulfate, Water